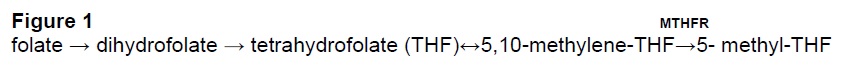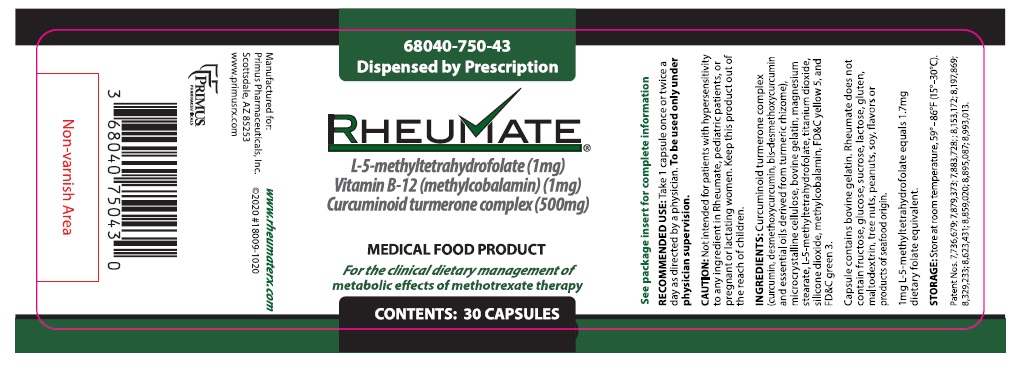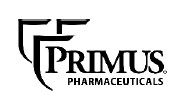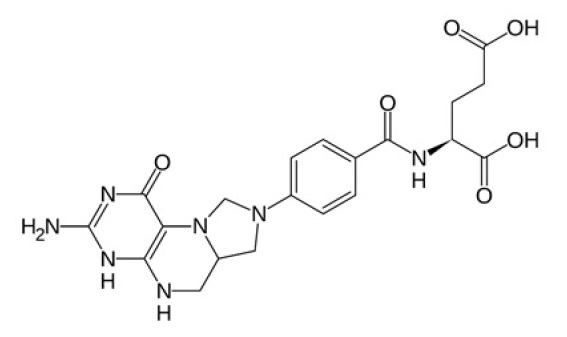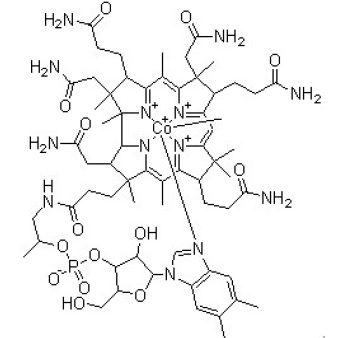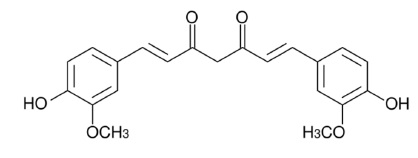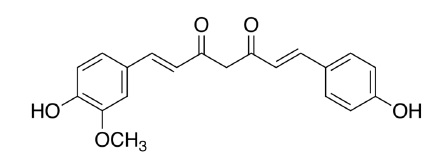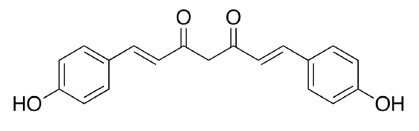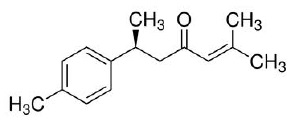 DRUG LABEL: Rheumate
NDC: 68040-750 | Form: CAPSULE
Manufacturer: Primus Pharmaceuticals, Inc.
Category: other | Type: MEDICAL FOOD
Date: 20250303

ACTIVE INGREDIENTS: METHYLCOBALAMIN 1 mg/1 1; LEVOMEFOLIC ACID 1 mg/1 1; CURCUMINOIDS 500 mg/1 1
INACTIVE INGREDIENTS: MICROCRYSTALLINE CELLULOSE; GELATIN TYPE B BOVINE (150 BLOOM); MAGNESIUM STEARATE; TITANIUM DIOXIDE; SILICON DIOXIDE; FD&C YELLOW NO. 5; FD&C GREEN NO. 3

Product Information
RHEUMATE® Capsules for oral administration.

Dispensed by prescription.

L-5-methyltetrahydrofolate 1 mg

Methylcobalamin (vitamin B-12) 1 mg

Curcuminoid turmerone complex 500 mg

1mg L-5-methyltetrahydrofolate equals 1.7mg dietary folate equivalent.

RHEUMATE is a specially formulated prescription medical food product for the clinical dietary management of metabolic effects of methotrexate therapy administered to patients with chronic inflammatory diseases. RHEUMATE must be administered under physician supervision.

DESCRIPTION

RHEUMATE consists of a proprietary mixture of L-5-methyltetrahydrofolate((6S)-5-methyltetrahydrofolic acid, methylcobalamin (vitamin B-12) and curcuminoid turmerone complex (high purity curcuminoids comprised of curcumin, desmethoxycurcumin, bis-desmethoxycurcumin and essential oils derived from turmeric rhizome).Reduced folate is required for one-carbon metabolic cycles. L-5-methyltetrahydrofolate addresses the methotrexate-induced distinctive nutritional requirement for folate due to competitive inhibition of reduced folate production, which may be more pronounced in people with a genetic polymorphism in the folate metabolic pathway. Methylcobalamin provides adequate vitamin B-12 stores to avoid masking borderline deficiency of B-12 with exogenous folate use. Curcumin helps to address the increased nutritional requirement for antioxidants associated with methotrexate induced oxidative stress.

L-5-methyltetrahydrofolate ((6S)-5-methyltetrahydrofolic acid) is chemically described as N-[4-[[[(6S)-2-amino-1,4,5,6,7,8-hexa-5-methyl-4-oxo-6-pteridinyl]methyl]amino]benzoyl]-L-glutamic acid with a molecular weight of 817.8. The empirical formula for L-5-methyltetrahydrofolic acid is C20H23N7O6(C6H14NO5)2. The structural formula is:

Methylcobalamin

Methylcobalamin is chemically described as carbanide; cobalt(2+);[(2R,3S,4R,5S)-5-(5,6-dimethylbenzimidazol-1-yl)-4-hydroxy-2-(hydroxymethyl)oxolan-3-yl][(2R)-1-[3-[(1R,2R,3R,4Z,7S,9Z,12S,13S,14Z,17S,18S,19R)-2,13,18-tris(2-amino-2-oxoethyl)-7,12,17-tris(3-amino-3-oxopropyl)-3,5,8,8,13,15,18,19-octamethyl-2,7,12,17-tetrahydro- 1H-corrin-21-id-3-yl]propanoylamino]propan-2-yl] phosphate with a molecular weight of 1344.4. The empirical formula for methylcobalamin is C63H91CoN13O14P. The structural formula is:

Curcuminoid turmerone complex is a composition of three curcuminoids and an essential oil, all sourced from turmeric.

Curcumin is chemically described as (1E,6E)-1,7-bis(4-hydroxy-3-methoxyphenyl)hepta-1,6-diene-3,5-dione with a molecular weight of 368.4. The empirical formula for curcumin is C21H20O6. The structural formula is:

Desmethoxycurcumin is chemically described as (1E,4Z,6E)-5-hydroxy-7-(4-hydroxy-3-methoxyphenyl)-1-(4-hydroxyphenyl)hepta-1,4,6-trien-3-one with a molecular weight of 338.4. The empirical formula for desmethoxycurcumin is C20H18O5. The structural formula is:

Bis-desmethoxycurcumin is chemically described as (1E,6E)-1,7-bis(4- hydroxyphenyl)hepta-1,6-diene-3,5-dione with a molecular weight of 308.3. The empirical formula for Bis-desmethoxycurcumin is C19H16O4. The structural formula is:

ar-turmerone, an essential oil of turmeric, is chemically described as (6S)-2-methyl-6-(4-methylphenyl)hept-2-en-4-one with a molecular weight of 216.3. The empirical formula for ar-turmerone is C15H20O. The structural formula is:

Additional Contents

RHEUMATE also contains the following: microcrystalline cellulose, bovine gelatin, magnesium stearate, titanium dioxide, silicone dioxide, FD&C yellow 5, and FD&C green 3.

Capsule contains bovine gelatin. RHEUMATE does not contain fructose, glucose, sucrose, lactose, gluten, maltodextrin, tree nuts, peanuts, soy, or flavors or product of seafood origin.

Medical Foods

The U.S. Congress defined “medical food” in the Orphan Drug Act and Amendments of 1988 as “a food which is formulated to be consumed or administered enterally under the supervision of a physician, and which is intended for the specific dietary management of a disease or condition for which distinctive nutritional requirements, based on recognized scientific principles, are established by medical evaluation.” RHEUMATE has been developed, manufactured and labeled in accordance with the statutory definition of a medical food. RHEUMATE is to be used only under a physician’s supervision.

Safety of Rheumate Ingredients

The ingredients in RHEUMATE meet the U.S. Food and Drug Administration (FDA) safety standards for food products. Ingredients may be used in food if they are Generally Recognized as Safe (GRAS), approved food additives, or approved color additives for the intended use. A use of a food substance may be GRAS either through scientific procedures or, for a substance used in food before 1958, through experience based on common use in food. General recognition of safety through scientific procedures ordinarily is based on published studies (which may be corroborated by
unpublished studies and other data and information). General recognition of safety through experience based on common use in foods requires a substantial history of consumption for food use by a significant number of consumers before 1958. All ingredients in RHEUMATE are either GRAS, approved food additives, or approved color additives.

METHOTREXATE-INDUCED DISTINCT NUTRITIONAL REQUIREMENTS

Methotrexate is the most widely used disease modifying drug in the treatment of inflammatory diseases such as rheumatoid arthritis, psoriatic arthritis or psoriasis. However, as many as 30% of patients must discontinue or reduce dosage of methotrexate because of adverse effects of methotrexate due to the failure to meet the increased need for folate. Methotrexate associated adverse events leading to the increased need for folate involve interference with the 1-carbon methylation cycle and other enzymatic processes for which reduced folate is a cofactor. Competitive inhibition of dihydrofolate reductase (DHFR) by methotrexate results in depletion of endogenous reduced folate stores due to an increased need for folate. Methylcobalamin provides adequate vitamin B-12 stores to avoid masking borderline deficiency of B-12 with exogenous folate supplementation.

Methotrexate adverse events are thought to be due in large part to a disruption of cellular redox homeostasis (severe oxidative stress) with depletion of natural antioxidant mechanisms (SOD, GTH, catalase and other peroxidases) and marked rise in oxidative products such as thiobarbituric acid reactive substances (TBARS) and malondialdehyde. This creates increased nutritional requirement for exogenous antioxidants. This leads to a distinct nutritional requirement for compounds such as dietary polyphenols, e.g., curcuminoids, which are powerful anti-oxidants and induce augmentation of endogenous antioxidant mechanisms, thus reducing oxidative burden.

CLINICAL PHARMACOLOGY

L-5-methyltetrahydrofolate is the bioactive form of folate. It is well absorbed and able to participate without further metabolism in all biochemical processes for which folate is a cofactor.

Cobalamin

Cobalamin (vitamin B-12) is well absorbed under normal conditions. However, many older people as well as people with atrophic gastritis and gastric hypochlorhydria (reduced stomach acid production) may not absorb cobalamin properly. This defect can be overcome with ingestion of additional dietary B-12 except in people with autoimmune atrophic gastritis who must be supplemented with parenteral B-12.

Curcuminoids

Because curcuminoids are known to be poorly absorbed, various methods have been devised to increase absorption of the molecules. The proprietary mixture of purified curcuminoids and essential turmeric oil used in product RHEUMATE increases the absorption and serum retention time of the curcuminoids molecules approximately 7- fold (Antony 2006). None of the ingredients in RHEUMATE are known to affect bioavailability by interacting with each other.

Mechanism of Action

L-5-methyltetrahydrofolate

L-5-methyltetrahydrofolate addresses the distinctive nutritional requirement for folate of patients taking methotrexate for treatment of inflammatory diseases including, but not limited to, rheumatoid arthritis, psoriatic arthritis or psoriasis. Folate is an essential cofactor in the NADP/NADH dependent 1-carbon transformation system involving methionine, homocysteine and serine and side pathways of their metabolism. These reactions are important in the metabolism and biosynthesis of amino acids, nucleic acids, membrane lipids, cholesterol and neurotransmitters. A significant proportion of the general population, however, has one or another polymorphisms in the methyltetrahydrofolate reductase (MTHFR) gene which catalyzes the rate limiting final conversion of 5,10-MTHF into the active 5-MTHF and, therefore, require 5-MTHF rather than folic acid. At least 90 polymorphisms have been found in the MTHFR gene locus. The most common and important of these, found in up to 20% of people in the U.S. and up to 50% of Europeans, is the C677T polymorphism which in its various forms greatly reduces enzyme activity or renders the enzyme inactive. L-5-methyltetrahydrofolate is the bioactive form of folate. Substitution of folic acid with L-5-methyltetrahydrofolate salts that do not require 10-demethylation therefore may obviate the effect of these polymorphisms (Figure 1).

Methylcobalamin

Methylcobalamin is an essential cofactor in many folate dependent metabolic pathways and minor deficiencies in cobalamin may be obscured in the presence of supraphysiological folate levels. While this may suppress such clinical signs as megaloblastic anemia, it does not prevent neurological damage associated with B12 deficiency. Cobalamin supplementation provides sufficient vitamin B-12 to assure that L-5-methyltetrahydrofolate administration does not mask cobalamin deficiency.

Curcuminoids Antioxidant Effects

Methotrexate is a drug that results in an increased nutritional requirement for liver antioxidant capacity because it increases levels of oxidative species and depletes levels of endogenous antioxidants. A significant adverse event associated with methotrexate use is liver injury. Drug induced liver injury (DILI) and its most serious outcome, acute fulminating hepatic failure, involve, among other things, increased production of reactive oxygen species (ROS) and nitric oxide and severe depletion of endogenous antioxidants such as superoxide dismutase (SOD), peroxidases and glutathione (GSH). These oxidative mechanisms cause activation of NFkB and increased expression of TNFα and other downstream inflammatory molecules which enhance the inflammatory response and leads to activation of cellular apoptotic and fibrotic mechanisms. Curcumin is an excellent antioxidant that scavenges a variety of reactive oxygen species (ROS) and inhibits lipid peroxidation about 10-fold more than vitamin E. Curcumin reduces formation of ROS and nitric oxide, helps restore endogenous antioxidant levels toward normal, reduces markers of lipid peroxidation, and inhibits the activation of NFkB without affecting the levels of constitutively expressed NFkB.

Other Clinical Effects

Curcumin also possesses significant anti-inflammatory effects related to inhibition of multiple aspects of arachidonic acid metabolism including suppression of prostaglandin (PG) and leukotriene (LT) synthesis by cyclooxygenase (COX) and lipoxygenase (LOX) by blocking respective enzyme induction. Curcumin down-regulates COX-2 and 5-LOX, IL-1β and TNFα by suppression of NFκB transcription and pre-transcriptional translocation to the nucleus. Curcumin also modulates phospholipase A2 and blocks up-regulation of MMP-4 and COX-2 induced by TNF and IL-1. Leukotrienes are potent molecules that attract and activate leukocytes and promote their adhesion to vessel walls.

Animal Studies

Numerous animal studies have shown the ability of curcumin to protect against or reverse liver damage induced by hepatic toxins such as carbon tetrachloride, sodium arsenite and other experimental hepatotoxins. Similarly, curcumin significantly reduced the severity of hepatic damage induced by methotrexate, acetaminophen, and multidrug tuberculosis regimens (INH, rifampin, pyrazinamide, ethambutol). In these experiments, methotrexate induced fatty degeneration and necrosis of liver hepatocytes and sinusoidal cells, reduction of levels of the endogenous antioxidants catalase, SOD and GSH and elevation of malondialdehyde, a marker of lipid peroxidation. Administration of curcumin (100mg/kg I.P.) ameliorated all the biochemical abnormalities and histological changes by preserving adequate oxidative status in hepatic tissue.

TOXICITY

L-5-methyltetrahydrofolate

No toxicity issues have been reported from folate supplementation. However, care must be taken to assure adequate cobalamin repletion to avoid masking cobalamin deficiency by correcting megaloblastic hematologic abnormalities with folate while allowing progression of neurologic disease due to cobalamin deficiency.

Methylcobalamin

No safety issues related to cobalamin supplementation have been reported.

Curcuminoids

No significant curcumin toxicity has been reported. Acute doses as high as 12 gm and chronic doses of 10gm/d have been found to be safe. Dozens of human clinical trials have uniformly demonstrated the lack of toxicity from curcumin. Minor gastrointestinal complaints have occasionally been noted in these trials. A few in vitro studies suggest that curcumin may interfere with platelet aggregation.

SPECIAL POPULATIONS

Pregnancy and Nursing Women

The use of RHEUMATE during pregnancy and lactation is up to the individual physician.

There is limited published data on curcumin toxicity in animal models. These data generally do not report any significant adverse events although one rodent study noted slight reduction in neonatal weight. Curcumin toxicity during pregnancy has not been formally studied in humans.

Pediatrics

Curcumin toxicity in pediatric age groups has not been studied in humans so the decision to use RHEUMATE in children is up to the individual physician.

INDICATIONS AND USAGE

Indications

RHEUMATE is intended for the clinical dietary management of metabolic effects of methotrexate therapy administered to patients with chronic inflammatory diseases under physician supervision.

Usage

RHEUMATE should be taken as one capsule by mouth once or twice daily as directed by a physician.

PRECAUTIONS AND CONTRAINDICATIONS

Hypersensitivity

RHEUMATE is contraindicated in patients with known hypersensitivity to any of the ingredients in the product. See “ingredients” for a full list of ingredients.

Warnings

Folate may interfere with absorption of tetracycline. Patients receiving both RHEUMATE and tetracycline should take these medications at least one hour apart. Sulfasalazine, phenytoin, statins and some birth control medications may lower levels of serum folate and impair utilization of folate.

Over Dosage

Curcumin

Curcumin has been administered in doses as high as 12 gm daily without significant adverse events except for occasional reports of mild gastrointestinal upset. Higher doses have not been studied. There are no reports of folate or cobalamin over dosage.

HOW SUPPLIED

RHEUMATE is supplied in two-part green and yellow capsules with a smooth surface imprinted X502 on one side of the yellow body of the capsule and 52012 on the other side of the yellow body of the capsule supplied as:

Product # | Size
68040-750-43 | Bottles of 30 capsules
68040-750-08 | Carton of 10 capsules as a sample (Not For Resale)

STORAGE AND HANDLING

Store at room temperature, 59-86°F (15-30°C) [see USP Controlled Room Temperature]. Protect from light and moisture. RHEUMATE is supplied to pharmacies in a recyclable plastic bottle with a child-resistant cap. Dispense in a light-resistant container as defined in the USP/NF with a child-resistant closure.

Dispensed by prescription.

Distributed by:
Primus Pharmaceuticals, Inc.
Scottsdale, AZ 85253

(480) 483-1410
www.primusrx.com
www.rheumaterx.com

Patent Nos. 7,736,679; 7,879,373; 7,883,728; 8,153,172; 8,197,869; 8,329,233; 8,623,431; 8,859,020; 8,895.087; 8,993,013
© 2020 Primus Pharmaceuticals, Inc. All rights reserved. 18003-1020

PRINCIPAL DISPLAY PANEL

68040-750-43

Dispensed by Prescription

RHEYMATE®

L-5-methyltetrahydrofolate (1mg)
Vitamin B-12 (Methylcobalamin) (1mg)
Curcuminoid turmerone complex (500mg)

MEDICAL FOOD PRODUCT

For the clinical dietary management of metabolic effect of methotrexate therapys

CONTENTS: 30 CAPSULES